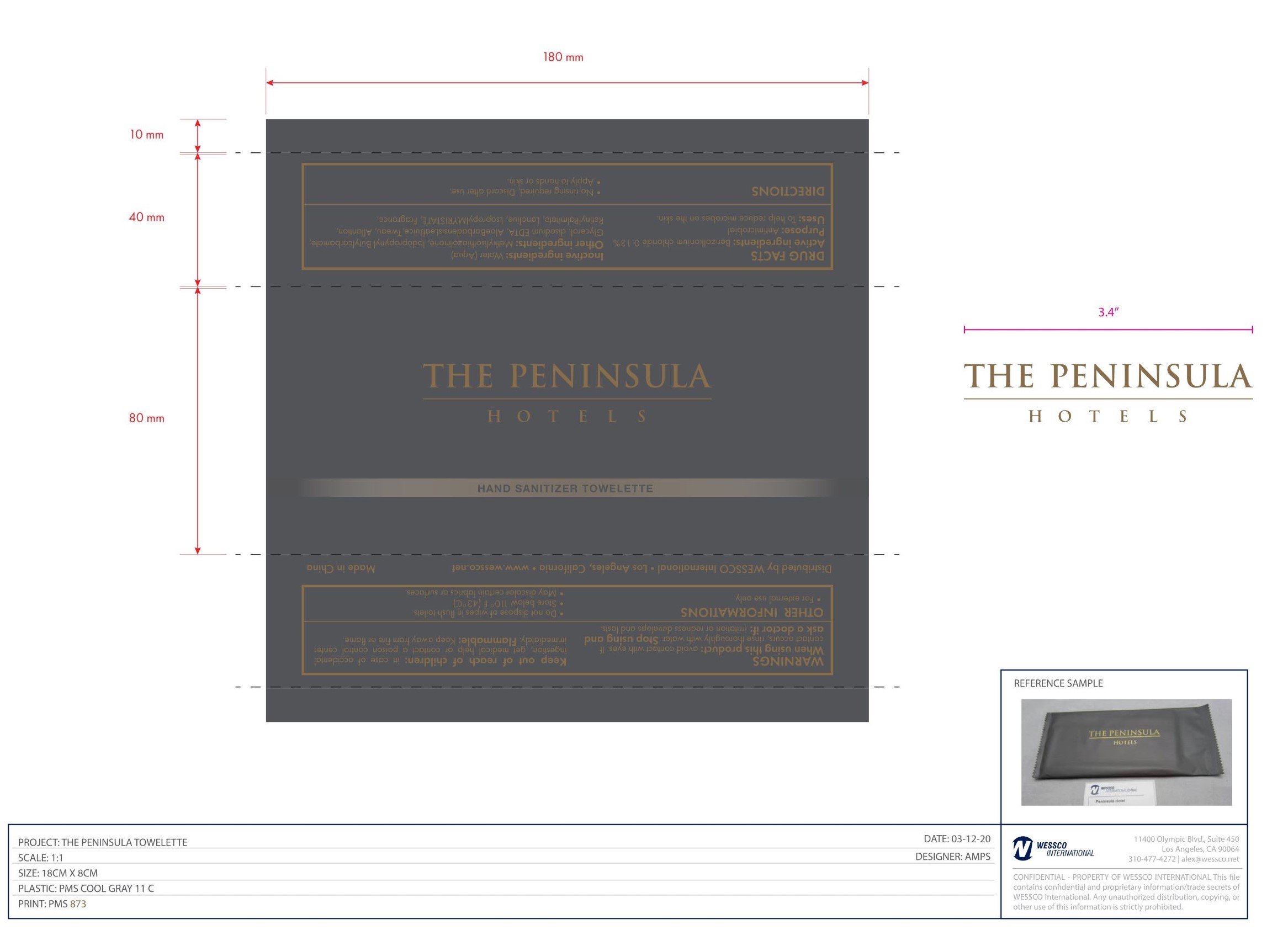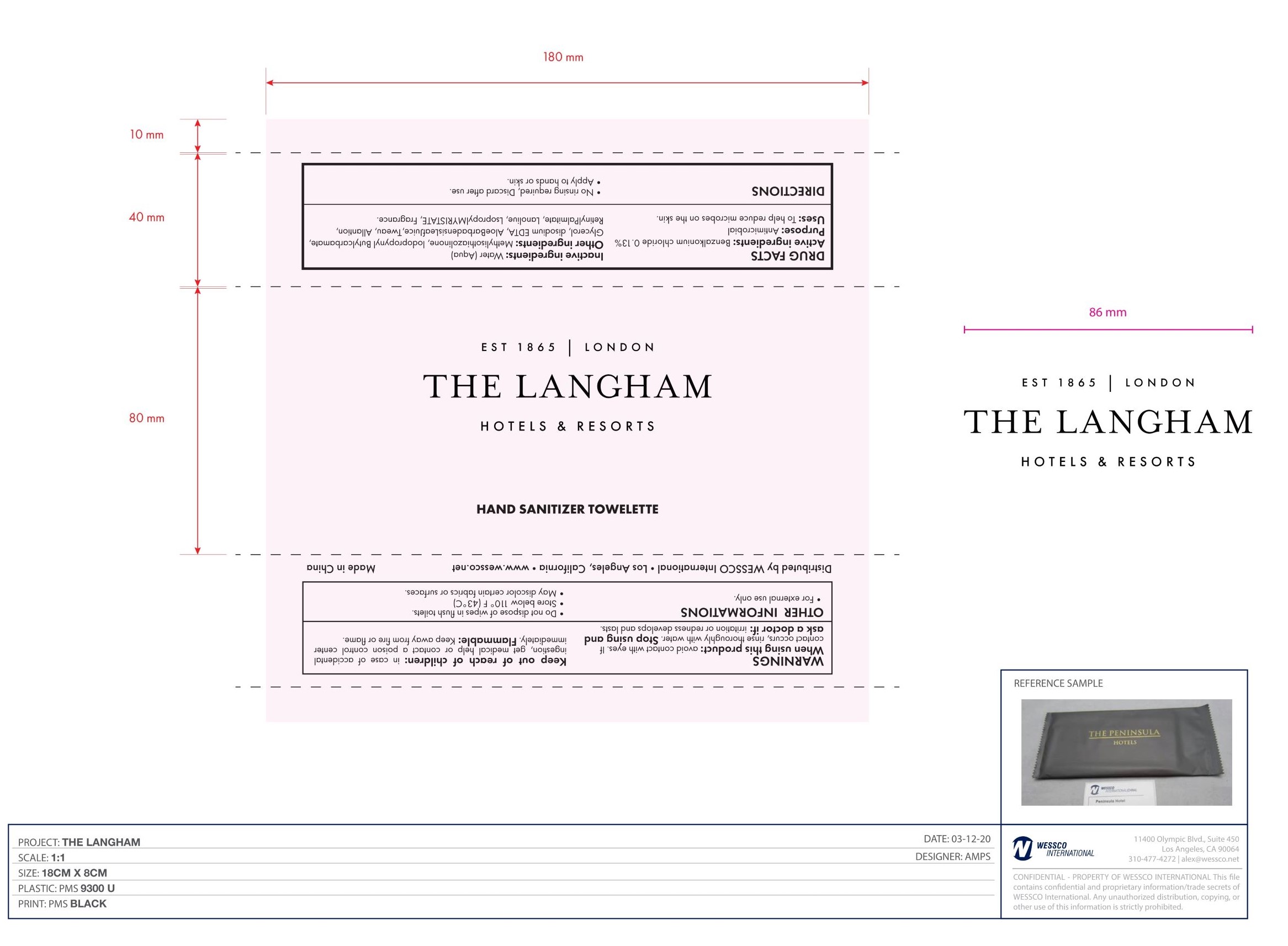 DRUG LABEL: HAND SANITIZER TOWELETTE
NDC: 42509-022 | Form: CLOTH
Manufacturer: WESSCO International
Category: otc | Type: HUMAN OTC DRUG LABEL
Date: 20200727

ACTIVE INGREDIENTS: BENZALKONIUM CHLORIDE 0.13 mg/100 mL
INACTIVE INGREDIENTS: GLYCERIN; LANOLIN; FRAGRANCE LEMON ORC2001060; WATER; METHYLISOTHIAZOLINONE; IODOPROPYNYL BUTYLCARBAMATE; EDETATE DISODIUM; POLYSORBATE 20; VITAMIN A PALMITATE; ISOPROPYL MYRISTATE; ALOE VERA LEAF; ALLANTOIN

WESSCO International
HAND SANITIZER TOWELETTE

Active Ingredient(s)

Benzalkonium chloride 0.13%

Purpose

Antimicrobial

Use

To help reduce microbes on the skin.

Warnings

- For external use only.
- Do not dispose of wipes in flush toilets.
- Flammable: Keep away from fire or flame.

When using this product: avoid contact with eyes. If contact occurs, rinse thoroughly with water.

STOP USE

Stop using and ask a doctor if: irritation or redness develops and lasts.

Keep out of reach of children: in case of accidental ingestion, get medical help or contact a poison control center immediately.

Directions

- No rinsing required, Discard after use.
- Apply to hands or skin.

Other information

- For external use only.
- Do not dispose of wipes in flush toilets.
- Store below 110° F (43°C)
- May discolor certain fabrics or surfaces.

Inactive ingredients

Water(Aqua), Methylisothiazolinone, lodopropynyl Butylcarbamate, Glycerol, disodium EDTA, AloeBarbadensisLeafJuice, Tweau, Allantion, RetinylPalmitate, Lanoliue, LsopropylMYRISTATE, Fragrance.

Package Label - Principal Display Panel

1pcs NDC: 42509-022-01

1pcs NDC: 42509-022-02